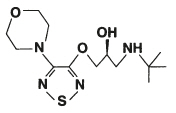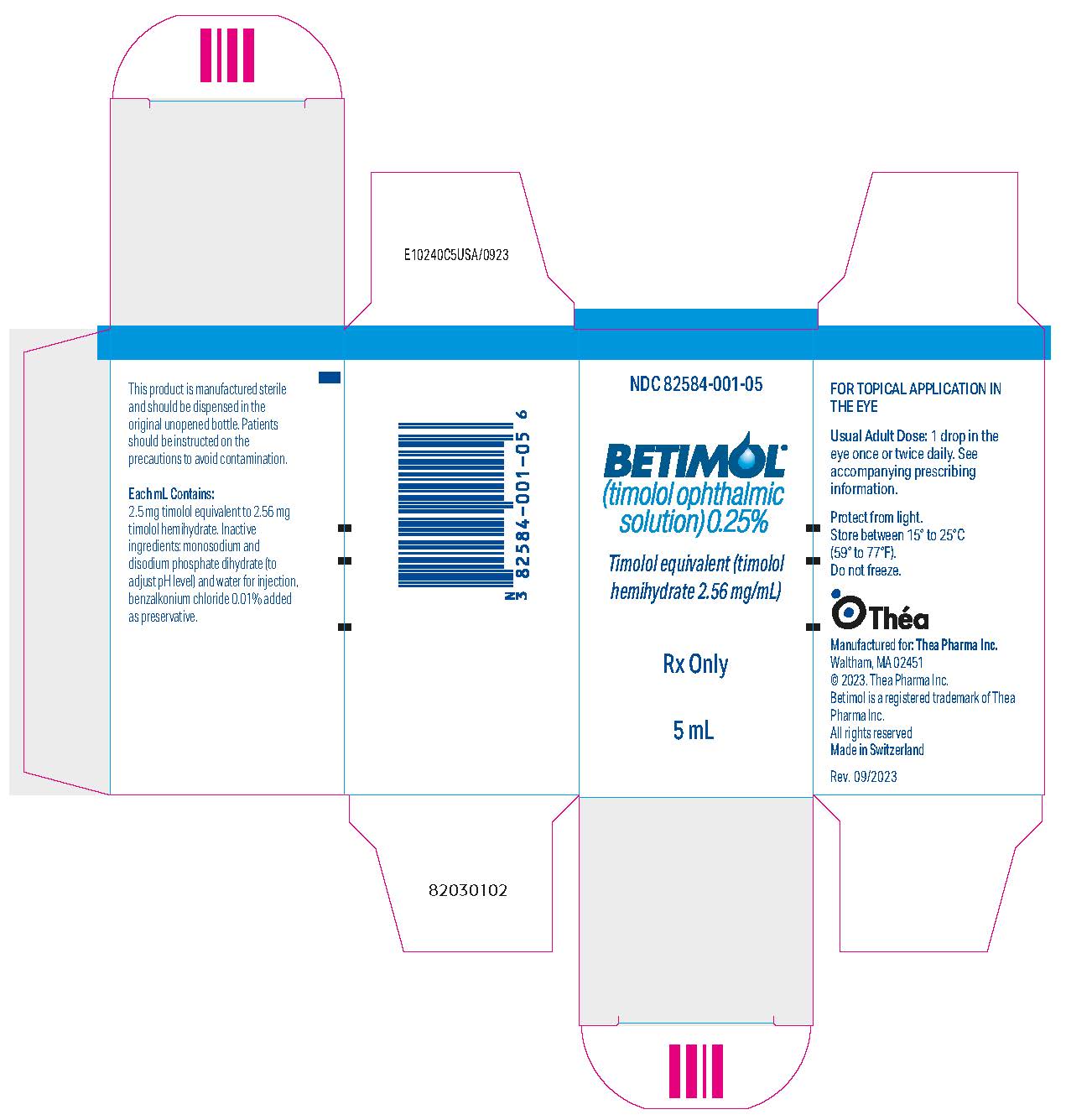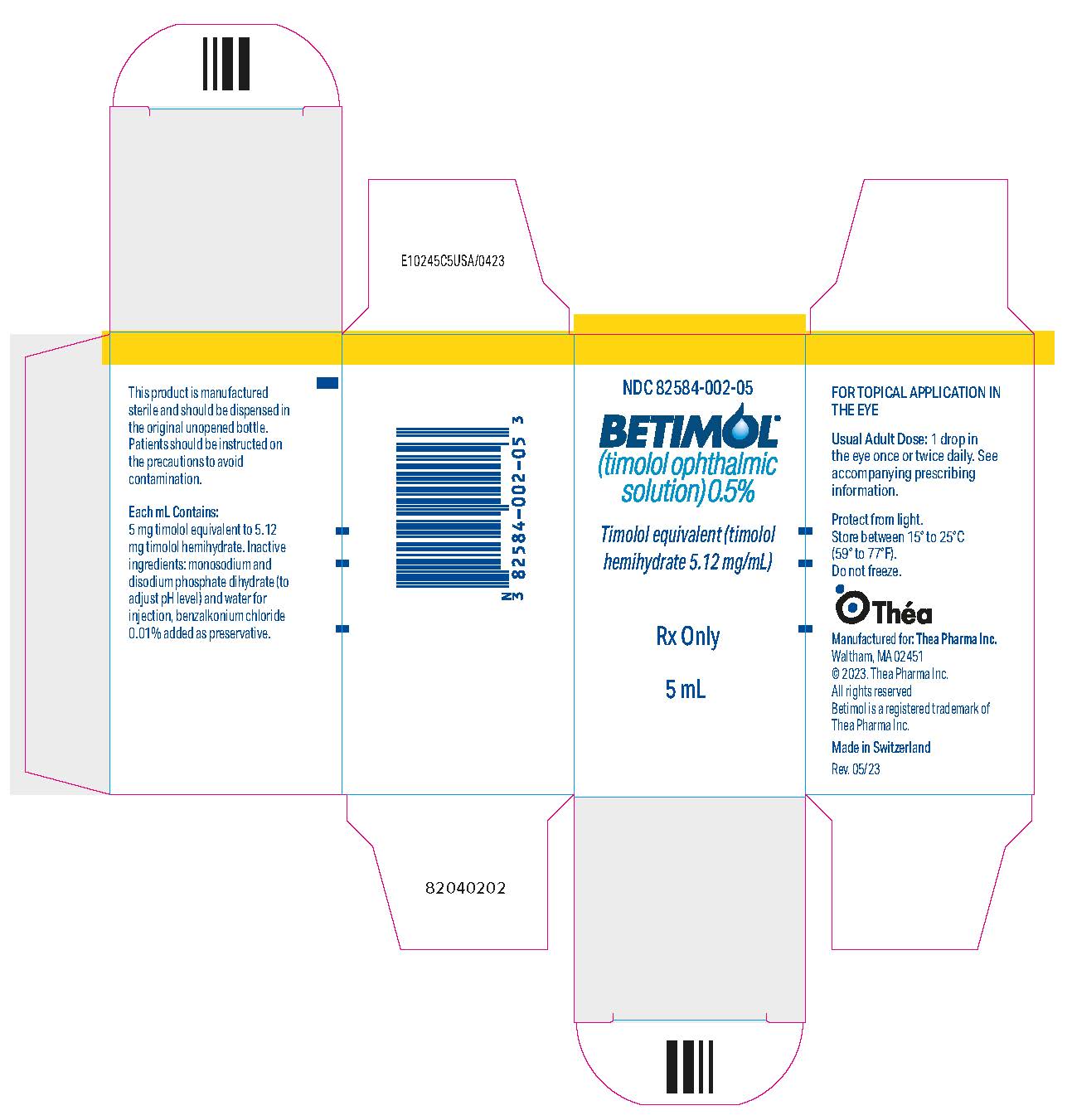 DRUG LABEL: BETIMOL
NDC: 82584-001 | Form: SOLUTION/ DROPS
Manufacturer: Thea Pharma Inc.
Category: prescription | Type: HUMAN PRESCRIPTION DRUG LABEL
Date: 20250627

ACTIVE INGREDIENTS: TIMOLOL 2.56 mg/1 mL
INACTIVE INGREDIENTS: SODIUM PHOSPHATE, MONOBASIC, DIHYDRATE; SODIUM PHOSPHATE, DIBASIC, DIHYDRATE; WATER; BENZALKONIUM CHLORIDE

BETIMOL®
(timolol ophthalmic
solution) 0.25%, 0.5%

DESCRIPTION

Betimol® (timolol ophthalmic solution), 0.25% and 0.5%, is a non-selective beta-adrenergic antagonist for ophthalmic use. The chemical name of the active ingredient is (S)-1-[(1, 1-dimethylethyl)amino]-3-[[4-(4-morpholinyl)-1,2,5-thiadiazol-3-yl]oxy]-2-propanol. Timolol hemihydrate is the levo isomer. Specific rotation is [α]^25 405nm=-16° (C=10% as the hemihydrate form in 1N HCl).

The molecular formula of timolol is Formula C13H24N4O3S and its structural formula is:

Timolol (as the hemihydrate) is a white, odorless, crystalline powder which is slightly soluble in water and freely soluble in ethanol. Timolol hemihydrate is stable at room temperature.

Betimol® is a clear, colorless, isotonic, sterile, microbiologically preserved phosphate buffered aqueous solution.

It is supplied in two dosage strengths, 0.25% and 0.5%.

Each mL of Betimol® 0.25% contains 2.56 mg of timolol hemihydrate equivalent to 2.5 mg timolol.

Each mL of Betimol® 0.5% contains 5.12 mg of timolol hemihydrate equivalent to 5.0 mg timolol.

Inactive ingredients: monosodium and disodium phosphate dihydrate to adjust pH (6.5 - 7.5) and water for injection, benzalkonium chloride 0.01 % added as preservative.

The osmolality of Betimol® is 260 to 320 mOsmol/kg.

CLINICAL PHARMACOLOGY

Timolol is a non-selective beta-adrenergic antagonist.

It blocks both beta1-and beta2-adrenergic receptors. Timolol does not have significant intrinsic sympathomimetic activity, local anesthetic (membrane-stabilizing) or direct myocardial depressant activity.

Timolol, when applied topically in the eye, reduces normal and elevated intraocular pressure (IOP) whether or not accompanied by glaucoma. Elevated intraocular pressure is a major risk factor in the pathogenesis of glaucomatous visual field loss. The higher the level of IOP, the greater the likelihood of glaucomatous visual field loss and optic nerve damage. The predominant mechanism of ocular hypotensive action of topical beta-adrenergic blocking agents is likely due to a reduction in aqueous humor production.

In general, beta-adrenergic blocking agents reduce cardiac output both in healthy subjects and patients with heart diseases. In patients with severe impairment of myocardial function, beta-adrenergic receptor blocking agents may inhibit sympathetic stimulatory effect necessary to maintain adequate cardiac function. In the bronchi and bronchioles, beta-adrenergic receptor blockade may also increase airway resistance because of unopposed parasympathetic activity.

Pharmacokinetics

When given orally, timolol is well absorbed and undergoes considerable first pass metabolism. Timolol and its metabolites are primarily excreted in the urine. The half-life of timolol in plasma is approximately 4 hours.

Clinical Studies

In two controlled multicenter studies in the U.S., Betimol® 0.25% and 0.5% were compared with respective timolol maleate eyedrops. In these studies, the efficacy and safety profile of Betimol® was similar to that of timolol maleate.

INDICATIONS AND USAGE

Betimol® is indicated in the treatment of elevated intraocular pressure in patients with ocular hypertension or open-angle glaucoma.

CONTRAINDICATIONS

Betimol® is contraindicated in patients with overt heart failure, cardiogenic shock, sinus bradycardia, second- or third-degree atrioventricular block, bronchial asthma or history of bronchial asthma, or severe chronic obstructive pulmonary disease, or hypersensitivity to any component of this product.

WARNINGS

As with other topically applied ophthalmic drugs, Betimol® is absorbed systemically. The same adverse reactions found with systemic administration of beta-adrenergic blocking agents may occur with topical administration. For example, severe respiratory and cardiac reactions, including death due to bronchospasm in patients with asthma, and rarely, death in association with cardiac failure have been reported following systemic or topical administration of beta-adrenergic blocking agents.

Cardiac Failure

Sympathetic stimulation may be essential for support of the circulation in individuals with diminished myocardial contractility, and its inhibition by beta-adrenergic receptor blockade may precipitate more severe cardiac failure.

In patients without a history of cardiac failure, continued depression of the myocardium with beta-blocking agents over a period of time can, in some cases, lead to cardiac failure. Betimol® should be discontinued at the first sign or symptom of cardiac failure.

Obstructive Pulmonary Disease

Patients with chronic obstructive pulmonary disease (e.g. chronic bronchitis, emphysema) of mild or moderate severity, bronchospastic disease, or a history of bronchospastic disease (other than bronchial asthma or a history of bronchial asthma which are contraindications) should in general not receive beta-blocking agents.

Major Surgery

The necessity or desirability of withdrawal of beta-adrenergic blocking agents prior to a major surgery is controversial. Beta-adrenergic receptor blockade impairs the ability of the heart to respond to beta-adrenergically mediated reflex stimuli. This may augment the risk of general anesthesia in surgical procedures. Some patients receiving beta-adrenergic receptor blocking agents have been subject to protracted severe hypotension during anesthesia. Difficulty in restarting and maintaining the heartbeat has also been reported. For these reasons, in patients undergoing elective surgery, gradual withdrawal of beta-adrenergic receptor blocking agents is recommended. If necessary during surgery, the effects of beta-adrenergic blocking agents may be reversed by sufficient doses of beta-adrenergic agonists.

Diabetes Mellitus

Beta-adrenergic blocking agents should be administered with caution in patients subject to spontaneous hypoglycemia or to diabetic patients (especially those with labile diabetes) who are receiving insulin or oral hypoglycemic agents. Beta-adrenergic receptor blocking agents may mask the signs and symptoms of acute hypoglycemia.

Thyrotoxicosis

Beta-adrenergic blocking agents may mask certain clinical signs (e.g. tachycardia) of hyperthyroidism. Patients suspected of developing thyrotoxicosis should be managed carefully to avoid abrupt withdrawal of beta-adrenergic blocking agents which might precipitate a thyroid storm.

PRECAUTIONS

General

Because of the potential effects of beta-adrenergic blocking agents relative to blood pressure and pulse, these agents should be used with caution in patients with cerebrovascular insufficiency. If signs or symptoms suggesting reduced cerebral blood flow develop following initiation of therapy with Betimol®, alternative therapy should be considered.

There have been reports of bacterial keratitis associated with the use of multiple dose containers of topical ophthalmic products. These containers had been inadvertently contaminated by patients who, in most cases, had a concurrent corneal disease or a disruption of the ocular epithelial surface. (See PRECAUTIONS, Information for Patients.)

Muscle Weakness

Beta-adrenergic blockade has been reported to potentiate muscle weakness consistent with certain myasthenic symptoms (e.g. diplopia, ptosis, and generalized weakness). Beta-adrenergic blocking agents have been reported rarely to increase muscle weakness in some patients with myasthenia gravis or myasthenic symptoms.

In angle-closure glaucoma, the goal of the treatment is to reopen the angle. This requires constricting the pupil. Betimol® has no effect on the pupil. Therefore, if timolol is used in angle-closure glaucoma, it should always be combined with a miotic and not used alone.

Anaphylaxis

While taking beta-blockers, patients with a history of atopy or a history of severe anaphylactic reactions to a variety of allergens may be more reactive to repeated accidental, diagnostic, or therapeutic challenge with such allergens. Such patients may be unresponsive to the usual doses of epinephrine used to treat anaphylactic reactions.

The preservative benzalkonium chloride may be absorbed by soft contact lenses. Patients who wear soft contact lenses should wait 5 minutes after instilling Betimol® before they insert their lenses.

Information for Patients

Patients should be instructed to avoid allowing the tip of the dispensing container to contact the eye or surrounding structures.

Patients should also be instructed that ocular solutions can become contaminated by common bacteria known to cause ocular infections. Serious damage to the eye and subsequent loss of vision may result from using contaminated solutions. (See PRECAUTIONS, General.)

Patients requiring concomitant topical ophthalmic medications should be instructed to administer these at least 5 minutes apart.

Patients with bronchial asthma, a history of bronchial asthma, severe chronic obstructive pulmonary disease, sinus bradycardia, second- or third-degree atrioventricular block, or cardiac failure should be advised not to take this product (See CONTRAINDICATIONS.)

Drug Interactions

Beta-adrenergic blocking agents

Patients who are receiving a beta-adrenergic blocking agent orally and Betimol® should be observed for a potential additive effect either on the intraocular pressure or on the known systemic effects of beta-blockade.

Patients should not usually receive two topical ophthalmic beta-adrenergic blocking agents concurrently.

Catecholamine-depleting drugs

Close observation of the patient is recommended when a beta-blocker is administered to patients receiving catecholamine-depleting drugs such as reserpine, because of possible additive effects and the production of hypotension and/or marked bradycardia, which may produce vertigo, syncope, or postural hypotension.

Calcium antagonists

Caution should be used in the co-administration of beta-adrenergic blocking agents and oral or intravenous calcium antagonists, because of possible atrioventricular conduction disturbances, left ventricular failure, and hypotension. In patients with impaired cardiac function, co-administration should be avoided.

Digitalis and calcium antagonists

The concomitant use of beta-adrenergic blocking agents with digitalis and calcium antagonists may have additive effects in prolonging atrioventricular conduction time.

Injectable Epinephrine

(See PRECAUTIONS, General, Anaphylaxis.)

Carcinogenesis, Mutagenesis, Impairment of Fertility

Carcinogenicity of timolol (as the maleate) has been studied in mice and rats. In a two-year study orally administrated timolol maleate (300mg/kg/day) (approximately 42,000 times the systemic exposure following the maximum recommended human ophthalmic dose) in male rats caused a significant increase in the incidence of adrenal pheochromocytomas; the lower doses, 25 mg or 100 mg/kg daily did not cause any changes.

In a life span study in mice the overall incidence of neoplasms was significantly increased in female mice at 500 mg/kg/day (approximately 71,000 times the systemic exposure following the maximum recommended human ophthalmic dose). Furthermore, significant increases were observed in the incidences of benign and malignant pulmonary tumors, benign uterine polyps, as well as mammary adenocarcinomas. These changes were not seen at the daily dose level of 5 or 50 mg/kg (approximately 700 or 7,000, respectively, times the systemic exposure following the maximum recommended human ophthalmic dose). For comparison, the maximum recommended human oral dose of timolol maleate is 1 mg/kg/day.

Mutagenic potential of timolol was evaluated in vivo in the micronucleus test and cytogenetic assay and in vitro in the neoplastic cell transformation assay and Ames test. In the bacterial mutagenicity test {Ames test) high concentrations of timolol maleate (5000 and 10,000 g/plate) statistically significantly increased the number of revertants in Salmonella typhimuriumTA100, but not in the other three strains tested. However, no consistent dose-response was observed nor did the number of revertants reach the double of the control value, which is regarded as one of the criteria for a positive result in the Ames test. In vivo genotoxicity tests (the mouse micronucleus test and cytogenetic assay) and in vitro the neoplastic cell transformation assay were negative up to dose levels of 800 mg/kg and 100 g/mL, respectively.

No adverse effects on male and female fertility were reported in rats at timolol oral doses of up to 150 mg/kg/day (21,000 times the systemic exposure following the maximum recommended human ophthalmic dose).

Pregnancy Teratogenic effects

Category C

Teratogenicity of timolol (as the maleate) after oral administration was studied in mice and rabbits. No fetal malformations were reported in mice or rabbits at a daily oral dose of 50 mg/kg (7,000 times the systemic exposure following the maximum recommended human ophthalmic dose). Although delayed fetal ossification was observed at this dose in rats, there were no adverse effects on postnatal development of offspring. Doses of 1000 mg/kg/day (142,000 times the systemic exposure following the maximum recommended human ophthalmic dose) were maternotoxic in mice and resulted in an increased number of fetal resorptions. Increased fetal resorptions were also seen in rabbits at doses of 14,000 times the systemic exposure following the maximum recommended human ophthalmic dose in this case without apparent maternotoxicity.

There are no adequate and well-controlled studies in pregnant women. Betimol® should be used during pregnancy only if the potential benefit justifies the potential risk to the fetus.

Nursing mothers

Because of the potential for serious adverse reactions in nursing infants from timolol, a decision should be made whether to discontinue nursing or to discontinue the drug, taking into account the importance of the drug to the mother.

Pediatric use

Safety and efficacy in pediatric patients have not been established.

ADVERSE REACTIONS

The most frequently reported ocular event in clinical trials was burning/stinging on instillation and was comparable between Betimol® and timolol maleate (approximately one in eight patients).

The following adverse events were associated with use of Betimol® in frequencies of more than 5% in two controlled, double-masked clinical studies in which 184 patients received 0.25% or 0.5% Betimol®:

OCULAR:

Dry eyes, itching, foreign body sensation, discomfort in the eye, eyelid erythema, conjunctival injection, and headache.

BODY AS A WHOLE:

Headache.

The following side effects were reported in frequencies of 1 to 5%:

OCULAR:

Eye pain, epiphora, photophobia, blurred or abnormal vision, corneal fluorescein staining, keratitis, blepharitis and cataract.

BODY AS A WHOLE:

Allergic reaction, asthenia, common cold and pain in extremities.

CARDIOVASCULAR:

Hypertension.

DIGESTIVE:

Nausea.

METABOLIC/NUTRITIONAL:

Peripheral edema.

NERVOUS SYSTEM/PSYCHIATRY:

Dizziness and dry mouth.

RESPIRATORY:

Respiratory infection and sinusitis.

In addition, the following adverse reactions have been reported with ophthalmic use of beta blockers:

OCULAR:

Conjunctivitis, blepharoptosis, decreased corneal sensitivity, visual disturbances including refractive changes, diplopia and retinal vascular disorder.

BODY AS A WHOLE:

Chest pain.

CARDIOVASCULAR:

Arrhythmia, palpitation, bradycardia, hypotension, syncope, heart block, cerebral vascular accident, cerebral ischemia, cardiac failure and cardiac arrest.

DIGESTIVE:

Diarrhea.

ENDOCRINE:

Masked symptoms of hypoglycemia in insulin dependent diabetics (See WARNINGS).

NERVOUS SYSTEM/PSYCHIATRY:

Depression, impotence, increase in signs and symptoms of myasthenia gravis and paresthesia.

RESPIRATORY:

Dyspnea, bronchospasm, respiratory failure and nasal congestion.

SKIN:

Alopecia, hypersensitivity including localized and generalized rash, urticaria.

OVERDOSAGE

No information is available on overdosage with Betimol®. Symptoms that might be expected with an overdose of a beta-adrenergic receptor blocking agent are bronchospasm, hypotension, bradycardia, and acute cardiac failure.

DOSAGE AND ADMINISTRATION

Betimol® Ophthalmic Solution is available in concentrations of 0.25% and 0.5%. The usual starting dose is one drop of 0.25% Betimol® in the affected eye(s) twice a day. If the clinical response is not adequate, the dosage may be changed to one drop of 0.5% solution in the affected eye(s) twice a day.

If the intraocular pressure is maintained at satisfactory levels, the dosage schedule may be changed to one drop once a day in the affected eye(s). Because of diurnal variations in intraocular pressure, satisfactory response to the once-a-day dose is best determined by measuring the intraocular pressure at different times during the day.

Since in some patients the pressure-lowering response to Betimol® may require a few weeks to stabilize, evaluation should include a determination of intraocular pressure after approximately 4 weeks of treatment with Betimol®.

Dosages above one drop of 0.5% Betimol® twice a day generally have not been shown to produce further reduction in intraocular pressure. If the patient's intraocular pressure is still not at a satisfactory level on this regimen, concomitant therapy with pilocarpine and other miotics, and/or epinephrine, and/or systemically administered carbonic anhydrase inhibitors, such as acetazolamide, can be instituted.

HOW SUPPLIED

Betimol® (timolol ophthalmic solution) is a clear, colorless solution.

Betimol® 0.25% is supplied in a white, opaque, plastic, ophthalmic dispenser bottle with a controlled drop tip as follows:

NDC 82584-001-05 | 5 mL | fill in 5 cc container

Betimol® 0.5% is supplied in a white, opaque, plastic, ophthalmic dispenser bottle with a controlled drop tip as follows:

NDC 82584-002-05 | 5 mL | fill in 5 cc container
NDC 82584-002-15 | 15 mL | fill in 15 cc container

Rx Only

STORAGE

Store between 15° to 25°C (59° to 77°F). Do not freeze. Protect from light.

Manufactured for: Thea Pharma Inc.
Waltham, MA 02451

Made in Switzerland

© 2023. Thea Pharma Inc. All rights reserved

Betimol is a registered trademark of Thea Pharma Inc.

N10240C5USA/0423

82040302

Revised: 3/2024

Thea Pharma Inc.

PRINCIPAL DISPLAY PANEL - 5 mL Bottle Carton

NDC 82584-001-05

BETIMOL®
(timolol ophthalmic
solution) 0.25%

Timolol equivalent (timolol
hemihydrate 2.56 mg/mL)

Rx Only

5 mL

PRINCIPAL DISPLAY PANEL - 5 mL Bottle Carton - NDC 82854-002-05

NDC 82584-002-05

BETIMOL®
(timolol ophthalmic
solution) 0.5%

Timolol equivalent (timolol
hemihydrate 5.12 mg/mL)

Rx Only

5 mL